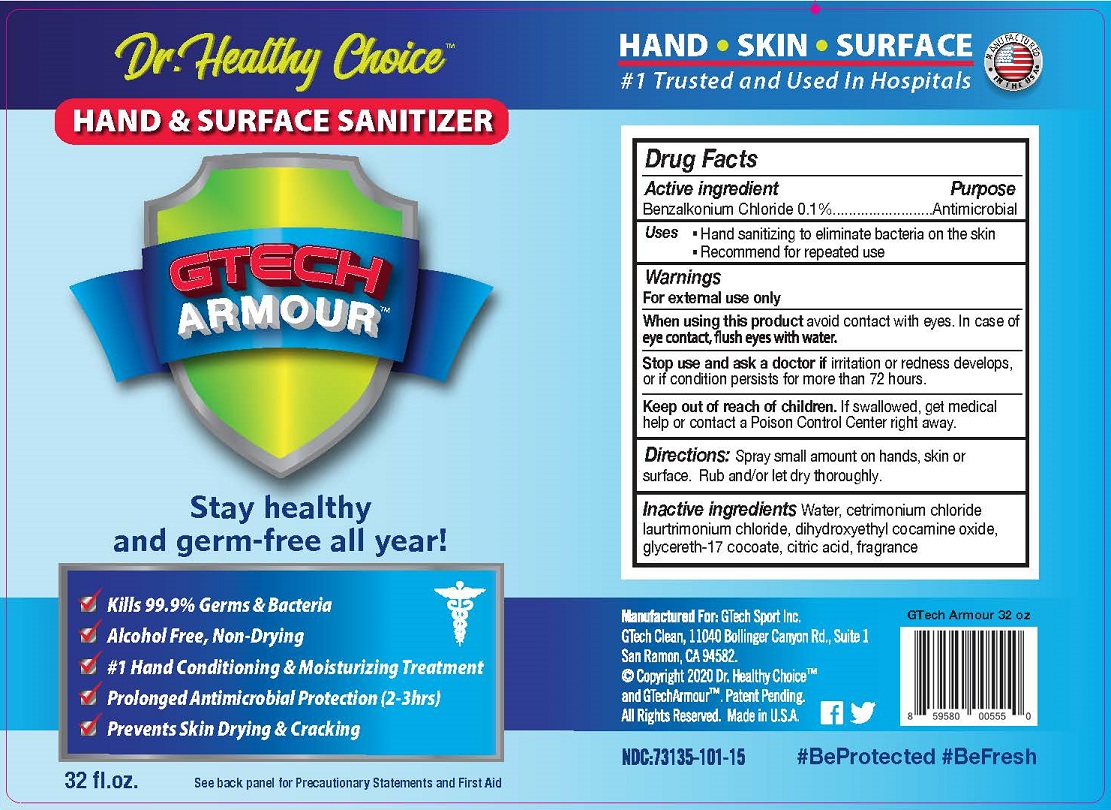 DRUG LABEL: DR. HEALTHY CHOICE HAND SANITIZER
NDC: 73135-101 | Form: SPRAY
Manufacturer: G Tech Sport
Category: otc | Type: HUMAN OTC DRUG LABEL
Date: 20220117

ACTIVE INGREDIENTS: BENZALKONIUM CHLORIDE 0.1 g/100 mL
INACTIVE INGREDIENTS: WATER; CETRIMONIUM CHLORIDE; LAURTRIMONIUM CHLORIDE; DIHYDROXYETHYL COCAMINE OXIDE; GLYCERETH-17 COCOATE; ANHYDROUS CITRIC ACID

G TECH SPORTS - DR. HEALTHY CHOICE HAND SANITIZER - GTECH ARMOUR (73135-101)

ACTIVE INGREDIENTS

BENZALKONIUM CHLORIDE 0.1%

PURPOSE

ANTIMICROBIAL

USES

- HAND SANITIZING TO ALLEVIATE BACTERIA ON THE SKIN
- RECOMMENDED FOR REPEATED USE

WARNINGS

FOR EXTERNAL USE ONLY.

WHEN USING THIS PRODUCT AVOID CONTACT WITH EYES. IN CASE OF EYE CONTACT, FLUSH EYES WITH WATER.

STOP USE AND ASK A DOCTOR IF IRRITATION OR REDNESS DEVELOPS, OR IF CONDITION PERSISTS FOR MORE THAN 72 HOURS.

KEEP OUT OF REACH OF CHILDREN. IF SWALLOWED, GET MEDICAL HELP OR CONTACT A POISON CONTROL CENTER RIGHT AWAY.

DIRECTIONS

SPRAY SMALL AMOUNT ON HANDS, SKIN OR SURFACES. RUB AND LET DRY THOROUGHLY.

INACTIVE INGREDIENTS

WATER, CETRIMONIUM CHLORIDE, LAURTRIMONIUM CHLORIDE, DIHYDROXYETHYL COCAMINE OXIDE, GLYCERETH-17 COCOATE, CITRIC ACID, FRAGRANCE